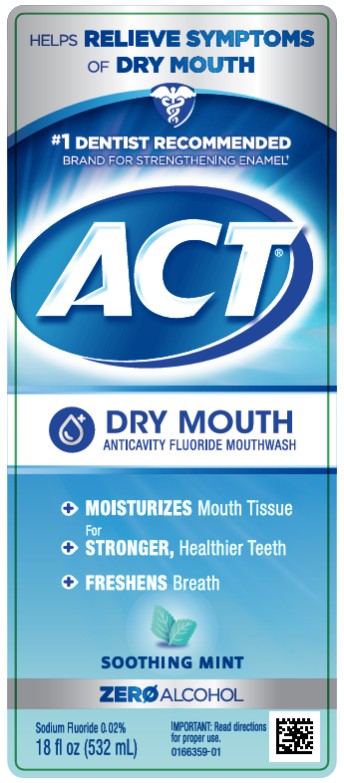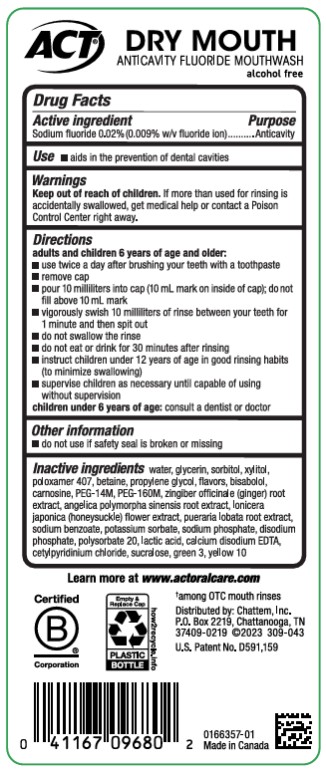 DRUG LABEL: ACT Total Care Dry Mouth Anticavity Mouth
NDC: 41167-0968 | Form: RINSE
Manufacturer: Chattem, Inc.
Category: otc | Type: HUMAN OTC DRUG LABEL
Date: 20241213

ACTIVE INGREDIENTS: SODIUM FLUORIDE 0.09 mg/1 mL
INACTIVE INGREDIENTS: WATER; GLYCERIN; SORBITOL; XYLITOL; POLOXAMER 407; BETAINE; PROPYLENE GLYCOL; LEVOMENOL; CARNOSINE; POLYETHYLENE OXIDE 600000; POLYETHYLENE OXIDE 7000000; GINGER; ANGELICA SINENSIS ROOT; LONICERA JAPONICA FLOWER; PUERARIA MONTANA VAR. CHINENSIS ROOT; SODIUM BENZOATE; POTASSIUM SORBATE; SODIUM PHOSPHATE; DISODIUM PHOSPHATE; POLYSORBATE 20; LACTIC ACID; EDETATE CALCIUM DISODIUM ANHYDROUS; CETYLPYRIDINIUM CHLORIDE; SUCRALOSE; FD&C GREEN NO. 3; D&C YELLOW NO. 10

ACT Total Care Anticavity Fluoride Rinse Dry Mouth

Drug Facts

Active ingredient

Sodium fluoride 0.02% (0.009% w/v fluoride ion)

Purpose

Anticavity

Use

- aids in the prevention of dental cavities

Warnings

Keep out of reach of children.

If more than used for rinsing is accidentally swallowed, get medical help or contact a Poison Control Center right away.

Directions

adults and children 6 years of age and older:

- use twice a day after brushing your teeth with a toothpaste
- remove cap
- pour 10 milliliters (10 mL mark on inside of cap); do not fill above 10 mL mark
- vigorously swish 10 milliliters of rinse between your teeth for 1 minute and then spit out
- do not swallow the rinse
- do not eat or drink for 30 minutes after rinsing
- instruct children under 12 years of age in good rinsing habits (to minimize swallowing)
- supervise children as necessary until capable of using without supervision

children under 6 years of age: consult a dentist or doctor

Other information

- do not use if safety seal is broken or missing

Inactive ingredients

water, glycerin, sorbitol, xylitol, poloxamer 407, betaine, propylene glycol, flavors, bisabolol, carnosine, PEG-14M, PEG-160M, zingiber officinale (ginger) root extract, angelica polymorpha sinensis root extract, lonicera japonica (honeysuckle) flower extract, pueraria lobata root extract, sodium benzoate, potassium sorbate, sodium phosphate, disodium phosphate, polysorbate 20, lactic acid, calcium disodium EDTA, cetylpyridinium chloride, sucralose, green 3, yellow 10 (309-043)

Learn more at www.ACTFLUORIDE.com

PRINCIPAL DISPLAY PANEL

#1 DENTIST RECOMMENDED
FLUORIDE BRAND
ACT® TOTAL CARE
ANTICAVITY FLUORIDE RINSE
DRY MOUTH
● SOOTHES Dry Mouth
● MOISTURIZES Mouth Tissue
● STRENGTHENS Teeth
● FRESHENS Breath
Sodium Fluoride 0.02%
18 fl oz (532 mL)